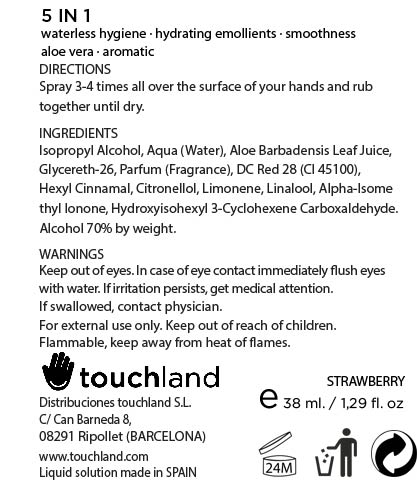 DRUG LABEL: TOUCHLAND kub2go Hand Sanitizer Strawberry
NDC: 70083-003 | Form: LIQUID
Manufacturer: Distribuciones Touchland S.L.
Category: otc | Type: HUMAN OTC DRUG LABEL
Date: 20150921

ACTIVE INGREDIENTS: ISOPROPYL ALCOHOL 0.7 mL/1 mL
INACTIVE INGREDIENTS: ALOE VERA LEAF; GLYCERETH-26; LIMONENE, (+)-; WATER; .ALPHA.-HEXYLCINNAMALDEHYDE; .BETA.-CITRONELLOL, (+/-)-; LINALOOL, (+)-; ISOMETHYL-.ALPHA.-IONONE; HYDROXYISOHEXYL 3-CYCLOHEXENE CARBOXALDEHYDE; D&C RED NO. 28

Active ingredient

Isopropyl alcohol 70% (W/W)

Directions

Spray 3-4 times all over the surface of your hands and rub together until dry. Supervise children in the use of this product.

Inactive ingredients

Aqua (Water), Aloe Barbadensis Leaf Juice, Glycereth-26, Parfum (Fragrance), D&C Red 28 (CI 45100), Hexyl Cinnamal, Citronellol, Limonene, Linalool, Alpha-Isomethyl Ionone, Hydroxyisohexyl 3-Cyclohexene Carboxaldehyde.

Warnings

Keep out of eyes. In case of eye contact immediately flush eyes with water. If irritation persists, get medical attention. If swallowed, contact physician.

For external use only. Keep out of reach of children.

Flammable, keep away from heat of flames.

Uses

Kills 99.99% of all disease causing germs on contact, and protects and restores moisture.

Purpose

Antiseptic